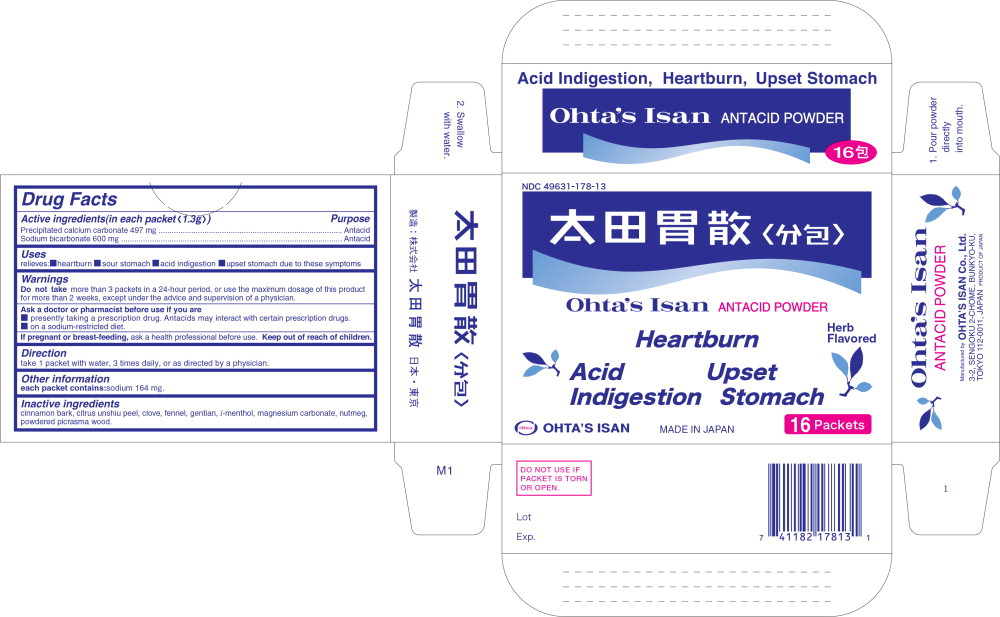 DRUG LABEL: OHTAS ISAN ANTACID
NDC: 49631-178 | Form: POWDER
Manufacturer: OHTA'S ISAN CO.,LTD.
Category: otc | Type: HUMAN OTC DRUG LABEL
Date: 20241021

ACTIVE INGREDIENTS: CALCIUM CARBONATE 1 g/1 g; SODIUM BICARBONATE 1 g/1 g
INACTIVE INGREDIENTS: CINNAMON; TANGERINE; CLOVE; FENNEL; GENTIANA LUTEA ROOT; LEVOMENTHOL; NUTMEG; PICRASMA QUASSIOIDES WOOD; MAGNESIUM CARBONATE

Drug Facts

Active ingredients (in each packet <1.3g>)

Precipitated calcium carbonate 497 mg

Sodium bicarbonate 600 mg

Purpose

Antacid

Antacid

Uses

relieves:

- heartburn
- sour stomach
- acid indigestion
- upset stomach due to these symptoms

Warnings

DO NOT USE

Do not take more than 3 packets in a 24-hour period, or use the maximum dosage of this product for more than 2 weeks, except under the advice and supervision of a physician.

Ask a doctor of a pharmacist before use if you are

- presently taking a prescription drug. Antacids may interact with certain prescription drugs.
- on a sodium-restricted diet.

PREGNANCY OR BREAST FEEDING

If pregnant or breast-feeding, ask a health professional before use.

Keep out of reach of children.

Direction

take 1 packet with water, 3 times daily, or as directed by a physician.

Other information

each packet contains: sodium 164 mg.

Inactive ingredients

cinnamon bark, citrus unshiu peel, clove, fennel, gentian, l-menthol, magnesium carbonate, nutmeg, powdered picrasma wood.

Principal Display Panel – 16 Packets Box Label

NDC 49631-178-13

Graphic – Ohta's Isan Logo

Ohta's Isan ANTACID POWDER

Heartburn Herb Flavored

Acid Upset

Indigestion Stomach

OHTA'S ISAN MADE IN JAPAN 16 Packets